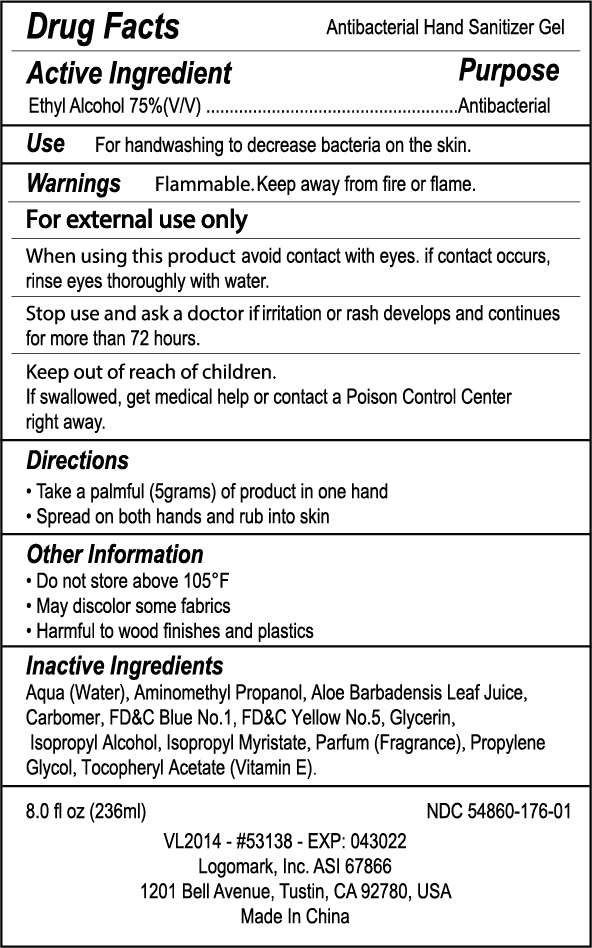 DRUG LABEL: hand sanitizer 236ml
NDC: 54860-176 | Form: LIQUID
Manufacturer: Shenzhen Lantern Science Co.,Ltd
Category: otc | Type: HUMAN OTC DRUG LABEL
Date: 20200418

ACTIVE INGREDIENTS: ALCOHOL 75 mL/100 mL
INACTIVE INGREDIENTS: ALOE VERA LEAF 0.1 mL/100 mL; ALOE 0.2 mL/100 mL; ISOPROPYL MYRISTATE 0.001 mL/100 mL; CARBOMER 940 0.4 mL/100 mL; WATER 23.057972 mL/100 mL; ISOPROPYL ALCOHOL 0.5 mL/100 mL; FD&C YELLOW NO. 5 0.00002 mL/100 mL; AMINOMETHYLPROPANOL 0.14 mL/100 mL; FD&C BLUE NO. 1 0.000008 mL/100 mL; GLYCERIN 0.5 mL/100 mL; PROPYLENE GLYCOL 0.1 mL/100 mL; .ALPHA.-TOCOPHEROL ACETATE 0.001 mL/100 mL

hand sanitizer 236ml

Active Ingredient

Active Ingredients Purpose

Ethyl Alcoh75% Antiseptic

USE

For handwashing to decrease bacteria on the skin.

DOSAGE AND ADMINISTRATION

Recommended for repeated use.

use anywhere without water.

Warning

flammable,keep away from fire or flame.

For external use only

When using this product,avoid contact with eyes.if contact occurs,rinse eyes thoroughly with water.

Stop use and ask a doctor if irritation or rash develops and continues for more than 72hours.

keep out of reach of children

If swallowed,get medical help or contact a Poison Control Center right away.

WARNINGS AND PRECAUTIONS

For external use only.

Flammable, keep away from heat and flame.

STOP USE

Discontinue if skin becomes irritated and ask a doctor .

Keep out of reach of children. In case of accidental ingestion, seek professional assistance or contact a poson control center immediately.

Inactive ingredients

Alcohol，Aqua(water)，Isopropyl Alcohol，Glycerin，Carbomer，Aminomethyl Propanol，Parfum(Fragrance)，Propylene Glycol，ISOPROPYL MYRISTATE，ALOE BARBADENSIS LEAF JUICE，Tocopheryl Acetate(Vitamin E)，FD&C Yellow No.5,FD&C Blue No.1.

Directions

Take a palmful(5grams) of product in one hand

spread on both hands and rub into skin

When using this product

keep out of eyes. In case of contact with eyes, flush thoroughly with water.

Do not inhale or ingest.

Avoid contact with broken skin.

Other information

Do not store above 105F.

May discolor some fabrics.

Harmful to wood finishes and plastics.

Other Information

Do not store above105℉

May discolor some fabrics

Harmful to wood finishes and plastics